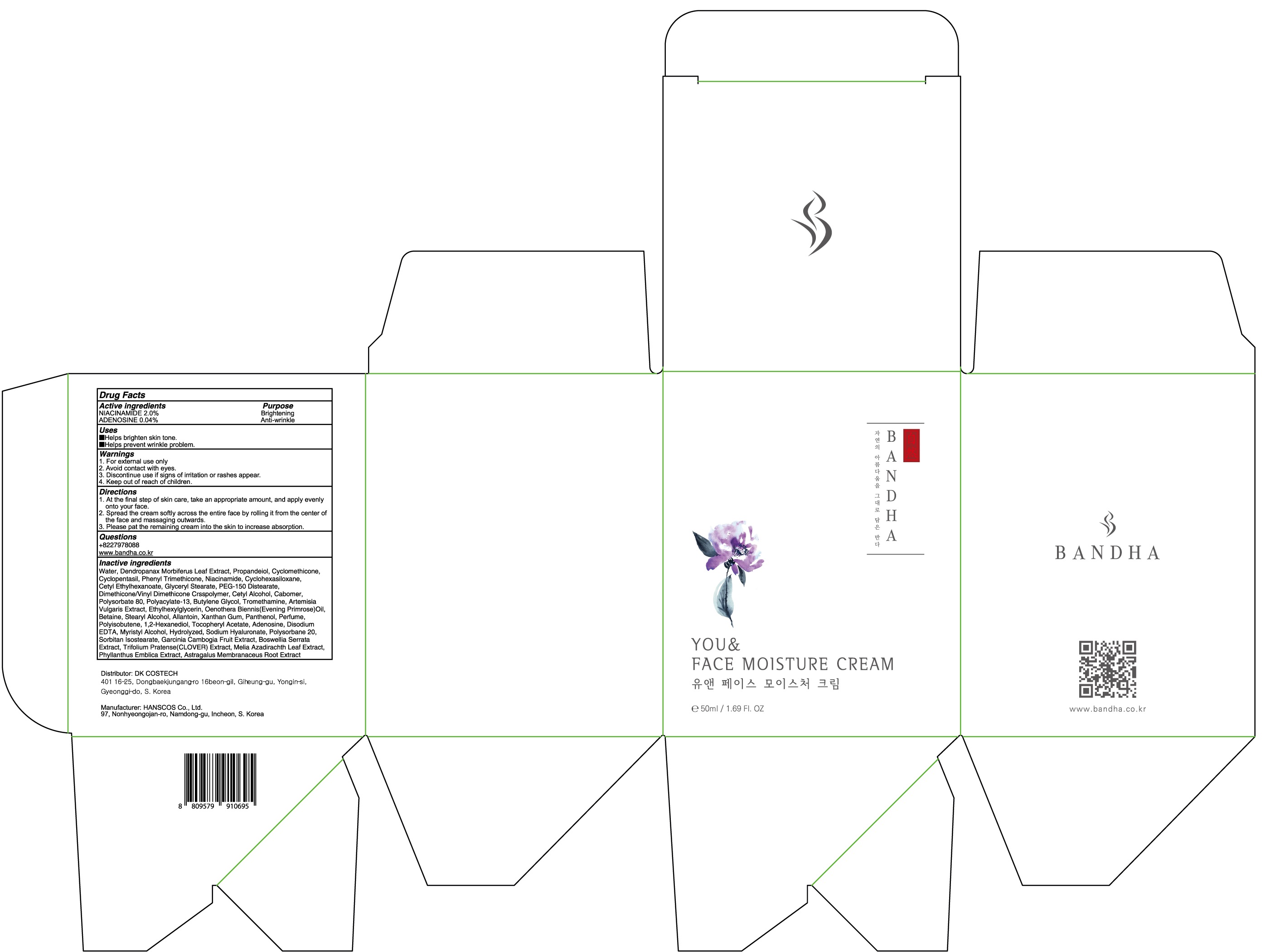 DRUG LABEL: BANDHA YOU AND FACE MOISTURE
NDC: 80623-040 | Form: CREAM
Manufacturer: DKCOSTECH
Category: otc | Type: HUMAN OTC DRUG LABEL
Date: 20200923

ACTIVE INGREDIENTS: NIACINAMIDE 1.0 g/50 mL; ADENOSINE 0.02 g/50 mL
INACTIVE INGREDIENTS: Water; Propanediol; CYCLOMETHICONE

ACTIVE INGREDIENTS

NIACINAMIDE 2.0%
ADENOSINE 0.04%

INACTIVE INGREDIENTS

Water, Dendropanax Morbiferus Leaf Extract, Propandeiol, Cyclomethicone, Cyclopentasil, Phenyl Trimethicone, Niacinamide, Cyclohexasiloxane,
Cetyl Ethylhexanoate, Glyceryl Stearate, Peg-150 Distearate, Dimethicone/Vinyl Dimethicone Crsspolymer, Cetyl Alcohol, Cabomer, Polysorbate 80, Polyacylate-13, Butylene Glycol, Tromethamine, Artemisia Vulgaris Extract, Ethylhexylglycerin, Oenothera Biennis(Evening Primrose)Oil,
Betaine, Stearyl Alcohol, Allantoin, Xanthan Gum, Panthenol, Perfume, Polyisobutene, 1,2-Hexanediol, Tocopheryl Acetate, Adenosine, Disodium EDTA, Myristyl Alcohol, Hydrolyzed, Sodium Hyaluronate, Polysorbane 20, Sorbitan Isostearate, Garcinia Cambogia Fruit Extract, Boswellia Serrata Extract, Trifolium Pratense(CLOVER) Extract, Melia Azadirachth Leaf Extract, Phyllanthus Emblica Extract, Astragalus Membranaceus Root Extract

PURPOSE

Brightening
Anti-wrinkle

WARNINGS

1. For external use only
2. Avoid contact with eyes.
3. Discontinue use if signs of irritation or rashes appear.
4. Keep out of reach of children.

KEEP OUT OF REACH OF CHILDREN

Uses

■ Helps brighten skin tone.
■ Helps prevent wrinkle problem.

Directions

1. At the final step of skin care, take an appropriate amount, and apply evenly onto your face.
2. Spread the cream softly across the entire face by rolling it from the center of the face and massaging outwards.
3. Please pat the remaining cream into the skin to increase absorption.

QUESTIONS

+8227978088
www.bandha.co.kr